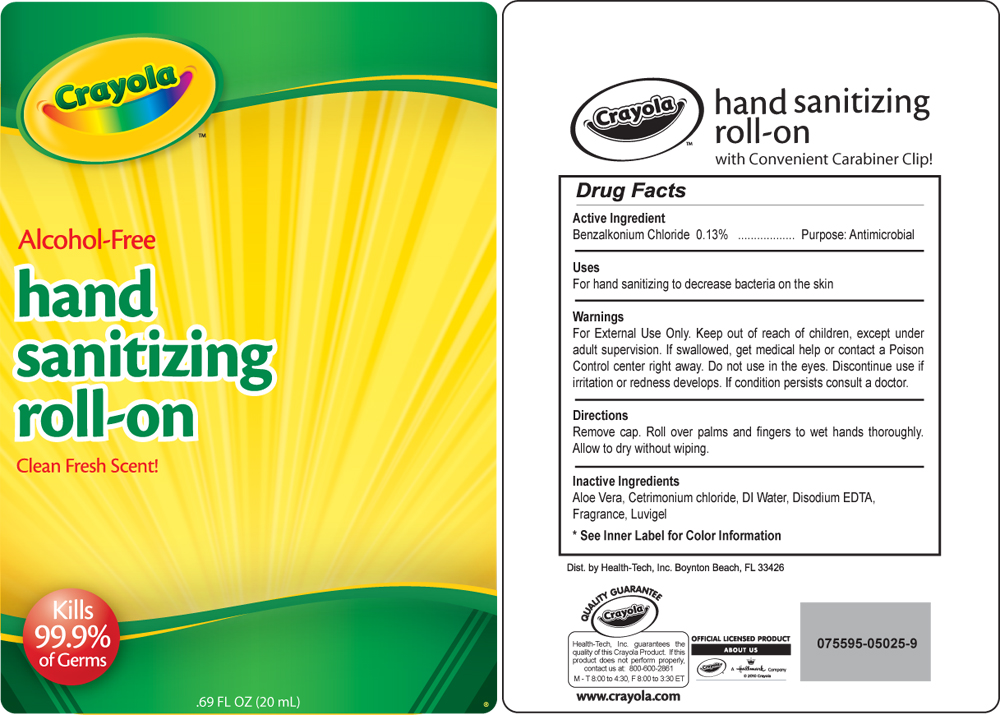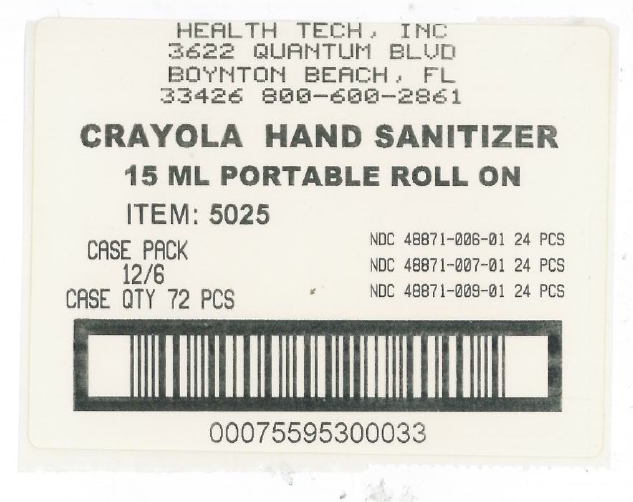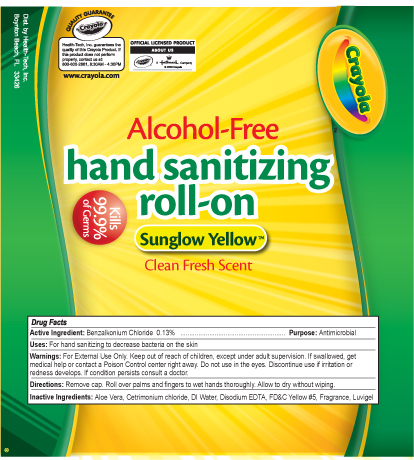 DRUG LABEL: Crayola Sunglow Yellow Roll On Hand Sanitizer
NDC: 48871-009 | Form: GEL
Manufacturer: Health-Tech, Inc.
Category: otc | Type: HUMAN OTC DRUG LABEL
Date: 20100525

ACTIVE INGREDIENTS: Benzalkonium Chloride .0013 mL/1 mL
INACTIVE INGREDIENTS: Aloe vera leaf; Cetrimonium Chloride; Edetate Disodium; water

Drug Facts

Active Ingredients

Active Ingredients: Benzalkonium Chloride - 0.13%

Purpose

Antimicrobial

Uses

For hand sanitizing to decrease bacteria on skin

WARNINGS

For external use only. Keep out of reach of children, except under adult supervision. If swallowed, get medical help or contact a Poison Control center right away. Do not use in the eyes. Discontinue use if irritation or redness develops. If condition persists, consult a doctor.

Directions

Remove cap. roll over palms and fingers to wet hands thoroughly. Allow to dry without wiping.

INACTIVE INGREDIENT

Aloe, Vera, Cetrimonium Chloride, Citrus Fragrance, Disodium EDTA, D and C red 33, FD and C yellow 5, Luvigel, Water

Crayola Sun Glow Yellow roll on label

MM20

Crayola blister card

MM21

Crayola roll on shipper label

MM17